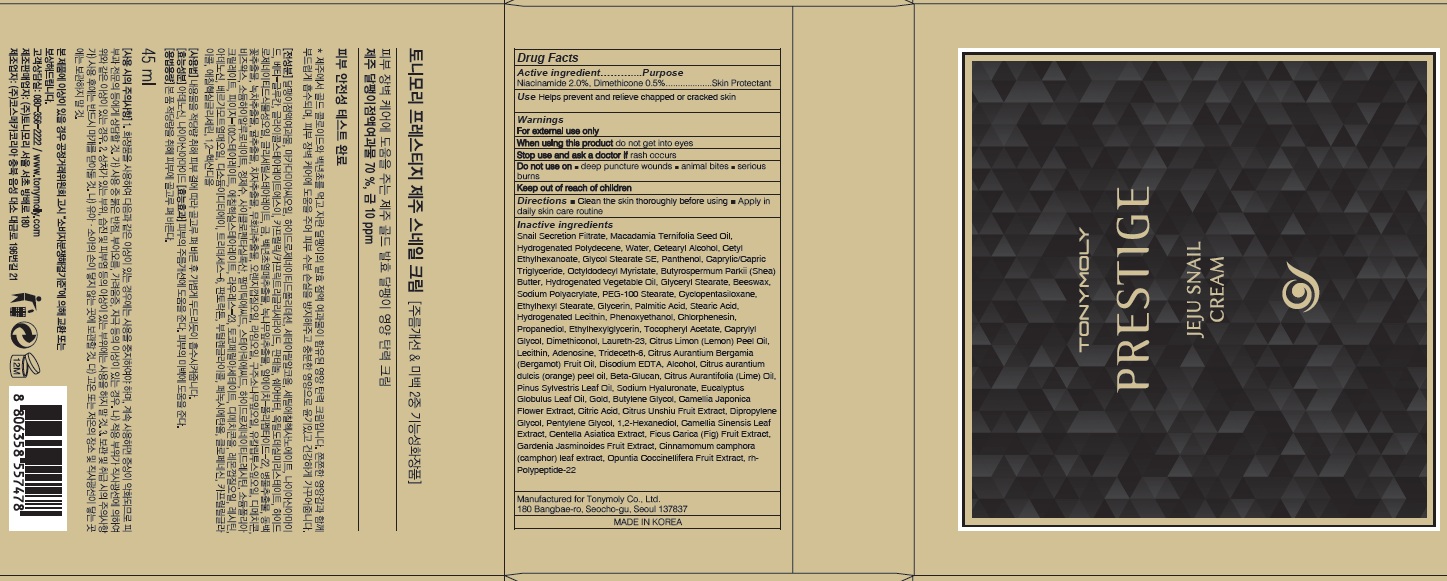 DRUG LABEL: PRESTIGE JEJU SNAIL
NDC: 59078-316 | Form: CREAM
Manufacturer: TONYMOLY CO.,LTD
Category: otc | Type: HUMAN OTC DRUG LABEL
Date: 20160729

ACTIVE INGREDIENTS: Niacinamide 0.90 g/45 mL; Dimethicone 0.22 g/45 mL
INACTIVE INGREDIENTS: Water; Panthenol

ACTIVE INGREDIENT

Active Ingredient: Niacinamide 2.0%, Dimethicone 0.5%

INACTIVE INGREDIENT

Inactive Ingredients: Snail Secretion Filtrate, Macadamia Ternifolia Seed Oil, Hydrogenated Polydecene, Water, Cetearyl Alcohol, Cetyl Ethylhexanoate, Glycol Stearate SE, Panthenol, Caprylic/Capric Triglyceride, Octyldodecyl Myristate, Butyrospermum Parkii (Shea) Butter, Hydrogenated Vegetable Oil, Glyceryl Stearate, Beeswax, Sodium Polyacrylate, PEG-100 Stearate, Cyclopentasiloxane, Ethylhexyl Stearate, Glycerin, Palmitic Acid, Stearic Acid, Hydrogenated Lecithin, Phenoxyethanol, Chlorphenesin, Propanediol, Ethylhexylglycerin, Tocopheryl Acetate, Caprylyl Glycol, Dimethiconol, Laureth-23, Citrus Limon (Lemon) Peel Oil, Lecithin, Adenosine, Trideceth-6, Citrus Aurantium Bergamia (Bergamot) Fruit Oil, Disodium EDTA, Alcohol, Citrus aurantium dulcis (orange) peel oil, Beta-Glucan, Citrus Aurantifolia (Lime) Oil, Pinus Sylvestris Leaf Oil, Sodium Hyaluronate, Eucalyptus Globulus Leaf Oil, Gold, Butylene Glycol, Camellia Japonica Flower Extract, Citric Acid, Citrus Unshiu Fruit Extract, Dipropylene Glycol, Pentylene Glycol, 1,2-Hexanediol, Camellia Sinensis Leaf Extract, Centella Asiatica Extract, Ficus Carica (Fig) Fruit Extract, Gardenia Jasminoides Fruit Extract, Cinnamomum camphora (camphor) leaf extract, Opuntia Coccinellifera Fruit Extract, rh-Polypeptide-22

PURPOSE

Purpose: Skin Protectant

WARNINGS

Warnings: For external use only When using this product do not get into eyes, Stop use and ask a doctor if rash occurs Do not use on - deep puncture wounds - animal bites - serious burns Keep out of reach of children

KEEP OUT OF REACH OF CHILDREN

Use

Use: Helps prevent and relieve chapped or cracked skin

Directions

Directions: - Clean the skin thoroughly before using - Apply in daily skin care routine